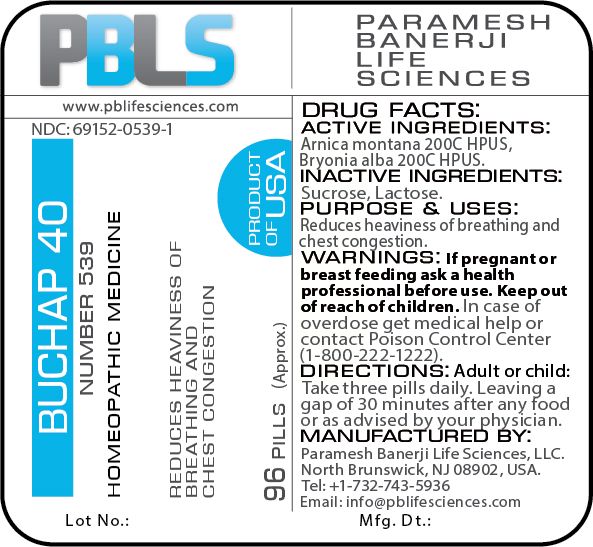 DRUG LABEL: Buchap 40 (Number 539)
NDC: 69152-0539 | Form: PELLET
Manufacturer: Paramesh Banerji Life Sciences LLC
Category: homeopathic | Type: HUMAN OTC DRUG LABEL
Date: 20180626

ACTIVE INGREDIENTS: BRYONIA ALBA ROOT 200 [hp_C]/1 1; ARNICA MONTANA 200 [hp_C]/1 1
INACTIVE INGREDIENTS: SUCROSE; LACTOSE

DRUG FACTS: Active Ingredients

Arnica montana 200C HPUS, Bryonia alba 200C HPUS

Inactive Ingredients

Sucrose, Lactose

Purpose

Reduces heaviness of breathing and chest congestion

Uses

Reduces heaviness of breathing and chest congestion

Warnings

If pregnant or breast feeding ask a health professional before use.

Keep out of reach of children. In case of overdose, get medical help or contact a Poison Control Center (1-800-222-1222) right away.

Direction

Adult or child: Take three pills daily. Leaving a gap of 30 minutes after any food or as advised by your physician.

Manufactured by

Paramesh Banerji Life Sciences, LLC.

North Brunswick, NJ 08902, USA.

Tel: +1-732-743-5936

Email: info@pblifesciences.com

Principal Display Panel

NDC: 69152-0539-1

Buchap 40

Number 539

Homeopathic Medicine

Reduces heaviness of breathing and chest congestion

96 Pills (Approx.)

Product of USA